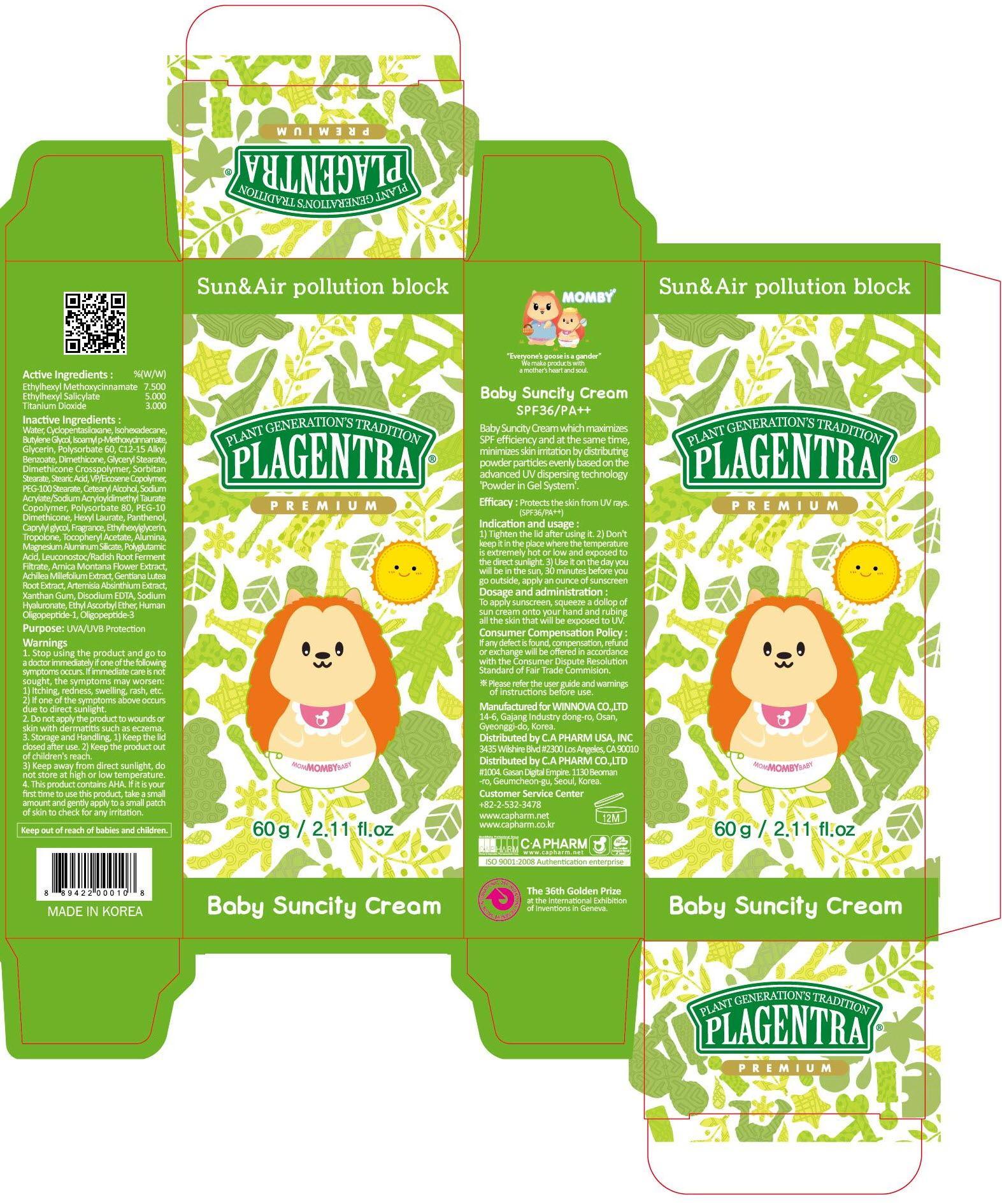 DRUG LABEL: PLAGENTRA BABY SUNCITY
NDC: 68988-090 | Form: CREAM
Manufacturer: C.A Pharm Co., Ltd.
Category: otc | Type: HUMAN OTC DRUG LABEL
Date: 20141208

ACTIVE INGREDIENTS: OCTINOXATE 4.5 g/60 g; OCTISALATE 3 g/60 g; TITANIUM DIOXIDE 1.8 g/60 g
INACTIVE INGREDIENTS: Water; Butylene Glycol

ACTIVE INGREDIENT

Active Ingredients: ETHYLHEXYL METHOXYCINNAMATE 7.5%, ETHYLHEXYL SALICYLATE 5.0%, TITANIUM DIOXIDE 3.0%

INACTIVE INGREDIENT

Inactive Ingredients:
Water, Cyclopentasiloxane, Isohexadecane, Butylene Glycol, Isoamyl p-Methoxycinnamate, Glycerin, Polysorbate 60, C12-15 Alkyl Benzoate, Dimethicone, Glyceryl Stearate, Dimethicone Crosspolymer, Sorbitan Stearate, Stearic Acid, VP/Eicosene Copolymer, PEG-100 Stearate, Cetearyl Alcohol, Sodium Acrylate/Sodium Acryloyldimethyl Taurate Copolymer, Polysorbate 80, PEG-10 Dimethicone, Hexyl Laurate, Panthenol, Caprylyl glycol, Fragrance, Ethylhexylglycerin, Tropolone, Tocopheryl Acetate, Alumina, Magnesium Aluminum Silicate, Polyglutamic Acid, Leuconostoc/Radish Root Ferment Filtrate, Arnica Montana Flower Extract, Achillea Millefolium Extract, Gentiana Lutea Root Extract, Artemisia Absinthium Extract, Xanthan Gum, Disodium EDTA, Sodium Hyaluronate, Ethyl Ascorbyl Ether, Human Oligopeptide-1, Oligopeptide-3

PURPOSE

Purpose: UVA/UVB Protection

WARNINGS

1. Stop using the product and go to a doctor immediately if one of the following symptoms occurs. If immediate care is not sought, the symptoms may worsen :
1) Itching, redness, swelling, rash, etc. 2) If one of the symptoms above occurs due to direct sunlight.
2. Do not apply the product to wounds or skin with dermatitis such as eczema.
3. Storage and Handling, 1) Keep the lid closed after use. 2) Keep the product out of children's reach. 3) Keep away from direct sunlight, do not store at high or low temperature.
4. It contains AHA. If it is your first time to use this product, take a small amount and gently apply to the skin to check if it cause andy trouble to your skin.

KEEP OUT OF REACH OF CHILDREN

Keep out of reach of babies and children.

INDICATIONS & USAGE

Indication and usage:
1) Tighten the lid after using it.
2) Don't keep it in the place where the temperature is extremely hot or low and exposed to the direct sunlight.
3) Use it on the day you will be in the sun, 30 minutes before you go outside, apply an ounce of sunscreen.

DOSAGE & ADMINISTRATION

Dosage and administration:
To apply sunscreen, squeeze a dollop of sun cream onto your hand and rub it all the skin that will be exposed to UV.